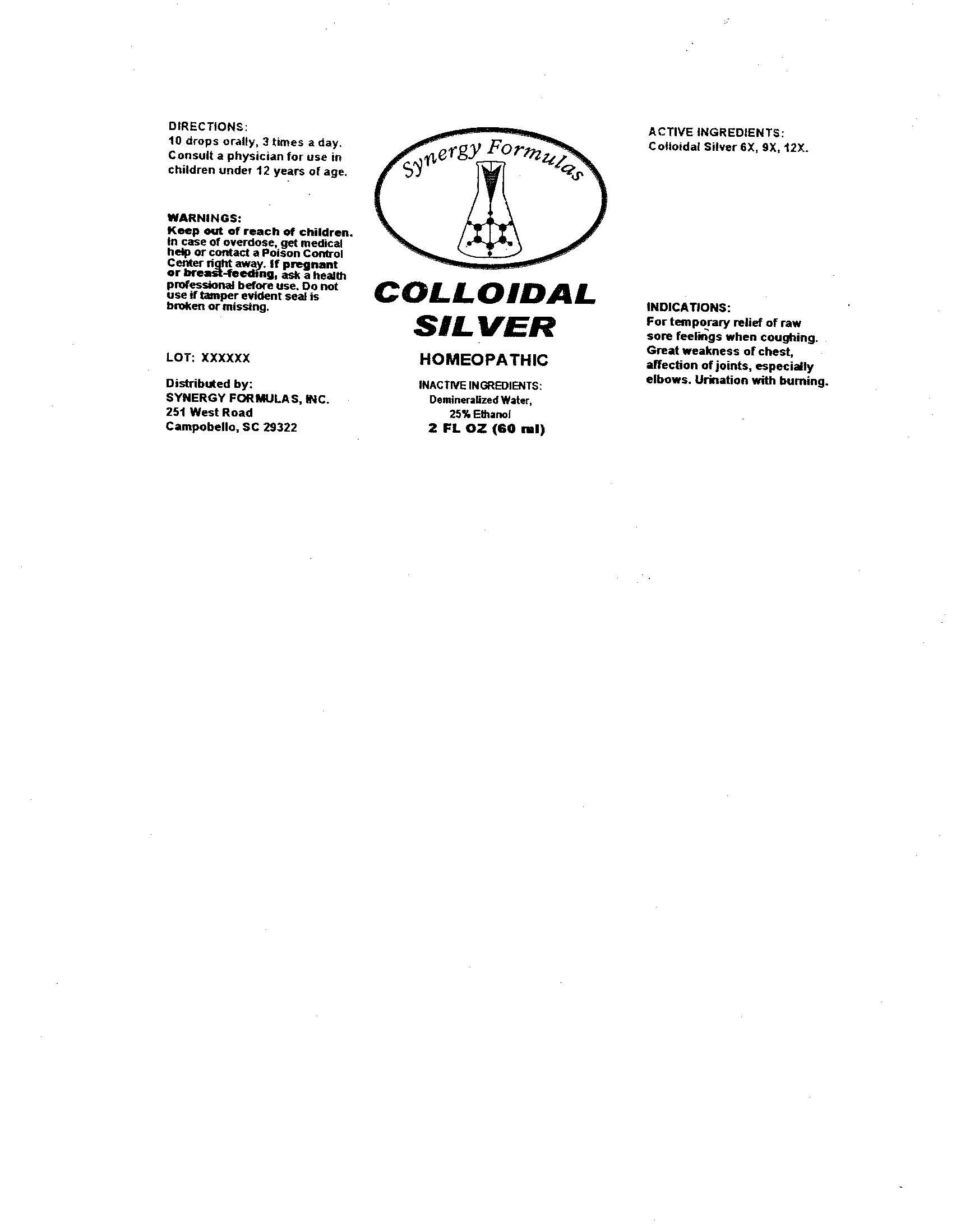 DRUG LABEL: Colloidal Silver
NDC: 57520-0322 | Form: LIQUID
Manufacturer: Apotheca Company
Category: homeopathic | Type: HUMAN OTC DRUG LABEL
Date: 20100723

ACTIVE INGREDIENTS: SILVER 12 [hp_X]/1 mL
INACTIVE INGREDIENTS: WATER; ALCOHOL

Colloidal Silver

ACTIVE INGREDIENTS: Colloidal silver 6X, 9X, 12X.

PURPOSE

INDICATIONS: For temporary relief of raw sore feelings when coughing. Great weakness of chest, affection of joints, especially elbows. Urination with burning.

WARNINGS

WARNINGS: Keep out of reach of children. In case of overdose, get medical help or contact a Poison Control Center right away.

If pregnant or breast-feeding, ask a health professional before use.

Do not use if tamper evident seal is broken or missing.

DOSAGE AND ADMINISTRATION

DIRECTIONS: 10 drops orally, 3 times a day. Consult a physician for use in children under 12 years of age.

INACTIVE INGREDIENTS: Demineralized Water, 25% Ethanol

QUESTIONS

Distributed By:

Synergy Formulas, Inc.

251 West Road

Campobello, SC 29322

PACKAGE LABEL

Synergy Formulas

COLLOIDAL SILVER

HOMEOPATHIC

2 FL OZ (60 ML)